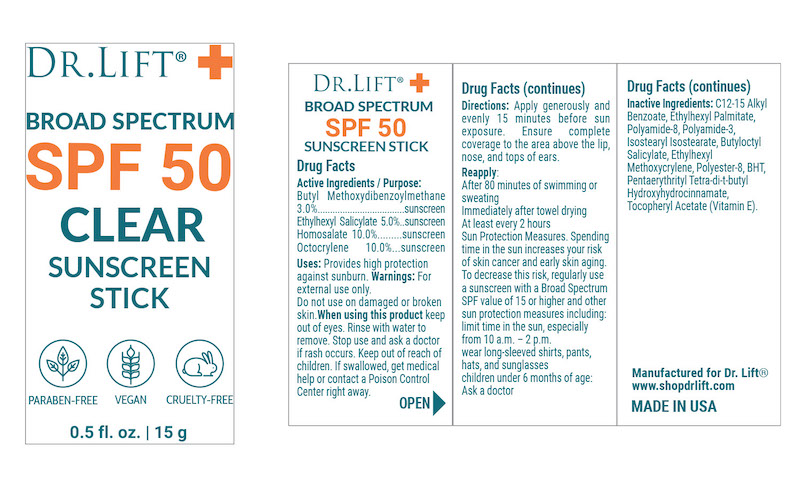 DRUG LABEL: Dr Lift SPF 50 Clear Stick
NDC: 68062-8313 | Form: STICK
Manufacturer: Spa de Soleil
Category: otc | Type: HUMAN OTC DRUG LABEL
Date: 20251009

ACTIVE INGREDIENTS: OCTISALATE 0.74 mg/14.8 mL; OCTOCRYLENE 1.48 mg/14.8 mL; AVOBENZONE 0.4 mg/14.8 mL; HOMOSALATE 1.48 mg/14.8 mL
INACTIVE INGREDIENTS: C12-15 ALKYL BENZOATE; ETHYLHEXYL PALMITATE; POLYAMIDE-8 (4500 MW); POLYAMIDE-3 (20000 MW); ISOSTEARYL ISOSTEARATE; BUTYLOCTYL SALICYLATE; ETHYLHEXYL METHOXYCRYLENE; POLYESTER-8 (1400 MW, CYANODIPHENYLPROPENOYL CAPPED); BHT; PENTAERYTHRITYL TETRA-DI-T-BUTYL HYDROXYHYDROCINNAMATE; .ALPHA.-TOCOPHEROL ACETATE, D-

Dr Lift SPF 50 Clear Stick

Active Ingredients

Butyl Methoxydibenzoylmethane 3.0%

Ethylhexyl Salicylate 5.0%

Homosalate 10.0%

Octocrylene 10.0%

Purpose

Sunscreen

Warnings

For external use only. Do not use on damaged or broken skin.When using this product keep out of eyes. Rinse with water to remove. Stop use and ask a doctor if rash occurs. Keep out of reach of children. If swallowed, get medical help or contact a Poison Control Center right away.

Keep out of reach of children.

DOSAGE AND ADMINISTRATION

Directions: Apply generously and evenly 15 minutes before sun exposure. Ensure complete coverage to the area above the lip, nose, and tops of ears.

Uses
Provides high protection against sunburn.

Inactive Ingredients

Inactive Ingredients: C12-15 Alkyl Benzoate, Ethylhexyl Palmitate, Polyamide-8, Polyamide-3, Isostearyl Isostearate, Butyloctyl Salicylate, Ethylhexyl Methoxycrylene, Polyester-8, BHT, Pentaerythrityl Tetra-di-t-butyl Hydroxyhydrocinnamate, Tocopheryl Acetate (Vitamin E).